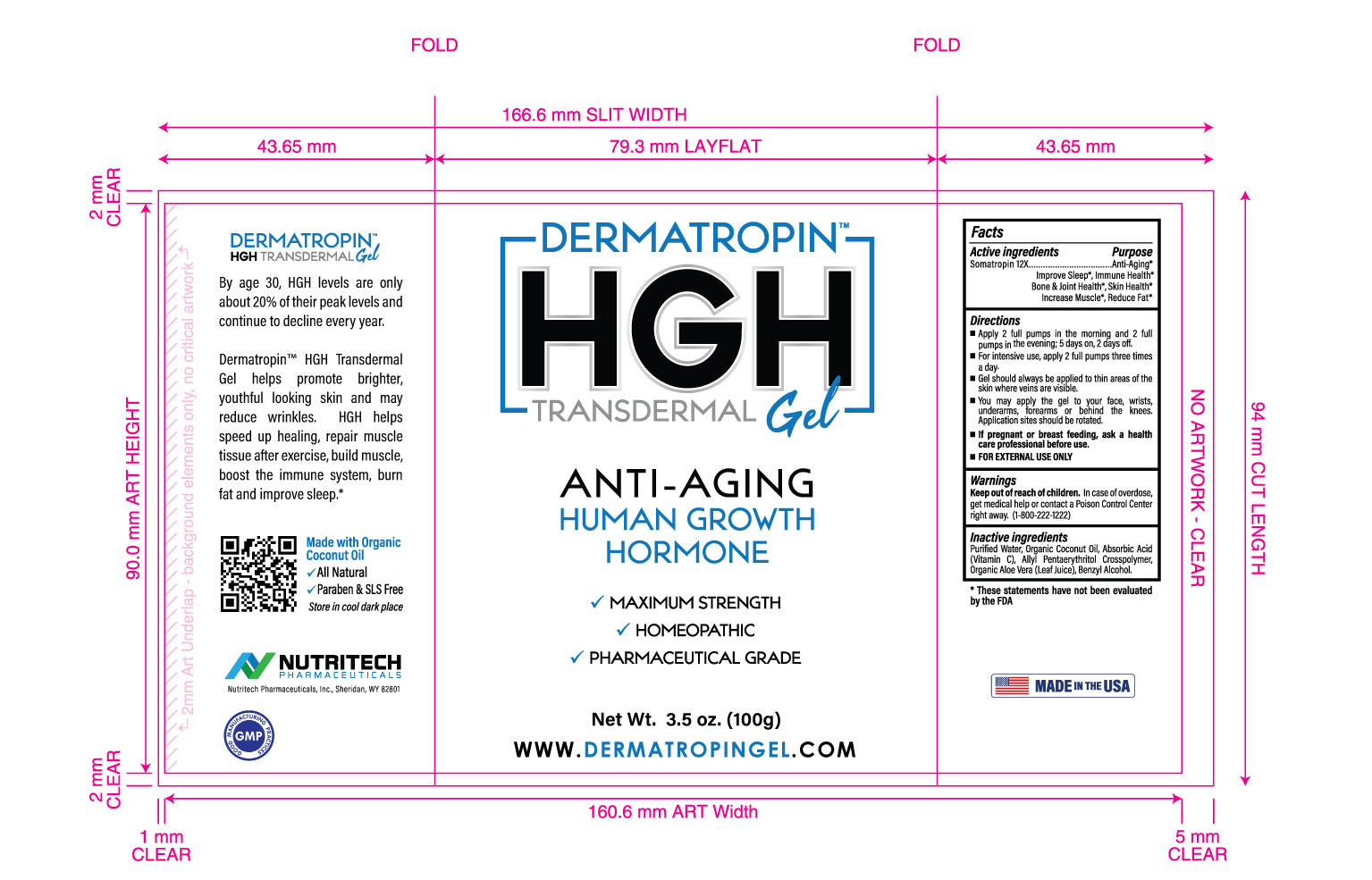 DRUG LABEL: Dermatropin
NDC: 73529-319 | Form: GEL
Manufacturer: Nutritech Pharmaceuticals, Inc.
Category: homeopathic | Type: HUMAN OTC DRUG LABEL
Date: 20200630

ACTIVE INGREDIENTS: SOMATROPIN 12 [hp_X]/1 g
INACTIVE INGREDIENTS: COCONUT OIL; CARBOMER HOMOPOLYMER TYPE C (ALLYL PENTAERYTHRITOL CROSSLINKED); ALOE VERA LEAF; ASCORBIC ACID; BENZYL ALCOHOL; WATER

Active Ingredients

Somatropin 12X

Purpose

Dermatropin™ HGH Transdermal Gel helps promotre brighter, youthful looking skin and may reduce wrinkles. HGH helps speed up healing, repair muscle tissue after exercise, build muscle, boost the immune system, burn fat and improve sleep.*

*These statements have not been evaluated by the FDA.

Directions

Apply 2 full pumps in the morning and 2 full pumps in the evening; 5 days on, 2 days off. For intensive use, apply 2 full pumps three times a day.

DOSAGE AND ADMINISTRATION

- Gel should always be applied to thin areas of the skin where veins are visible.
- You may apply the gel to your face, wrists, underarms, forearms or behind the knees. Application sites should be rotated.
- If pregnant or breast feeding, ask a health care professional before use.
- FOR EXTERNAL USE ONLY

Inactive Ingredients

Purified Water, Organic Coconut Oil, Absorbic Acid (Vitamin C), Allyl Pentaerythritol Crosspolymer, Organic Aloe Vera (Leaf Juice), Benzyl Alcohol.

Warnings

Keep out of reach of children.

WARNINGS

In case of overdose, get medical help or contact a Poison Control Center right away. (1-800-222-1222)

Package Label Display

Dermatropin™
HGH Transdermal Gel
Anti-Aging
Human Growth Hormone
Maximum Strength
Homeopathic
Pharmaceutical Grade

Net. Wt. 3.5oz. (100g)

www.dermatropingel.com